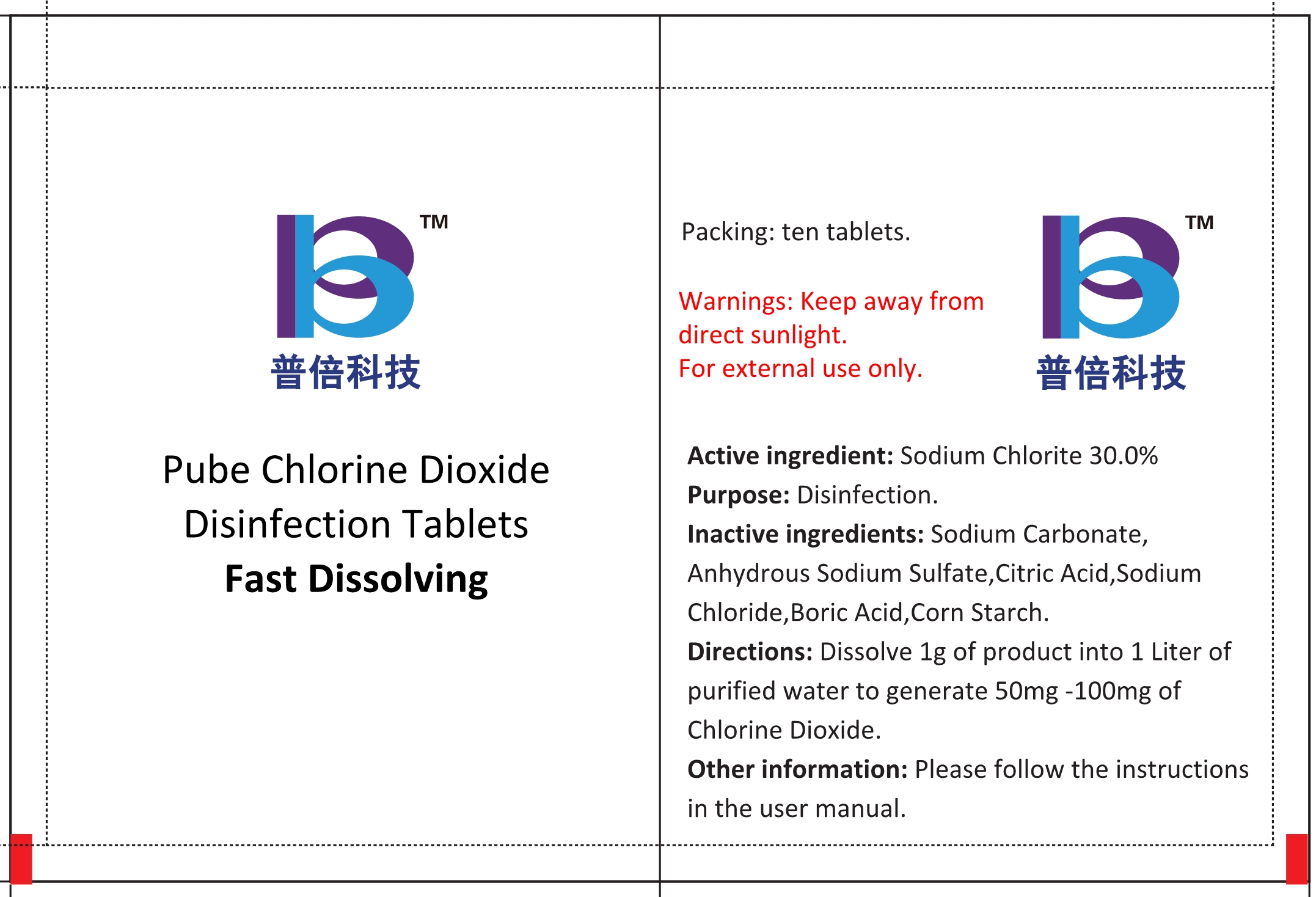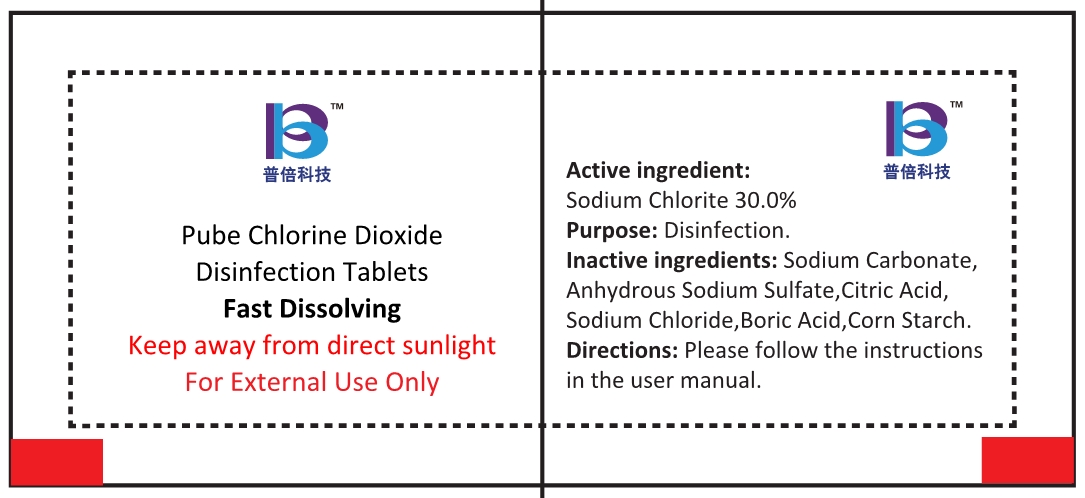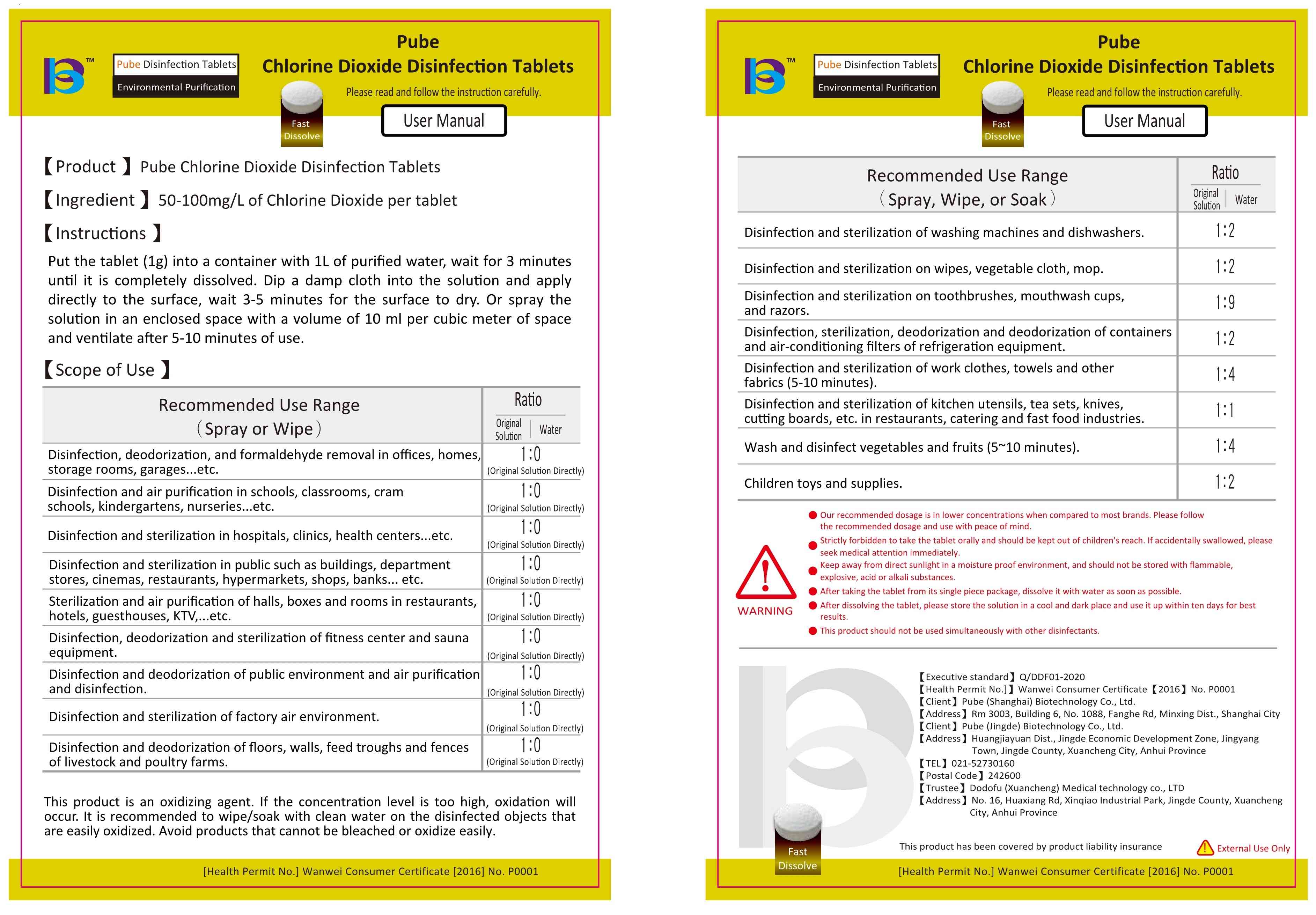 DRUG LABEL: Pube Chlorine Dioxide Disinfection
NDC: 81391-001 | Form: TABLET
Manufacturer: Guangdong Jiajie Technology Co., Ltd.
Category: otc | Type: HUMAN OTC DRUG LABEL
Date: 20240104

ACTIVE INGREDIENTS: SODIUM CHLORITE 30 g/100 g
INACTIVE INGREDIENTS: SODIUM CHLORIDE; STARCH, CORN; BORIC ACID; SODIUM SULFATE ANHYDROUS; CITRIC ACID MONOHYDRATE; SODIUM CARBONATE

81391-001
Meeting Zhuoma Tibetan Medicine YO Nano Superconducting Disinfection Factor
Pube Chlorine Dioxide Disinfection Tablets

Active Ingredient(s)

Sodium Chlorite 30.0%

Purpose

Disinfection.

Use

For external use only.

Warnings

Keep away from direct sunlight.
For external use only.

Do not use

/

WHEN USING

/

STOP USE

/

Directions

Dissolve 1g of product into 1 Liter of purified water to generate 50mg -100mg of Chlorine Dioxide.

Other information

Please follow the instructions in the user manual.

Inactive ingredients

Sodium Carbonate, Anhydrous Sodium Sulfate,Citric Acid,Sodium Chloride,Boric Acid,Corn Starch.

Package Label - Principal Display Panel

User Manual

81391-001-01 Outer packaging

81391-001-11 inner packaging